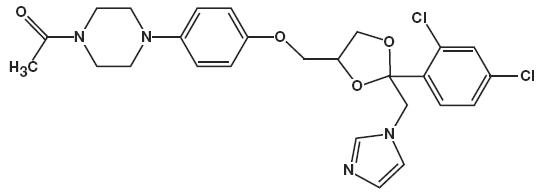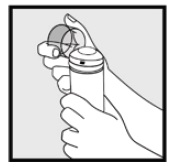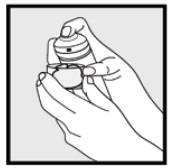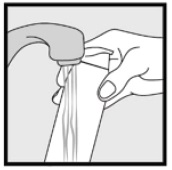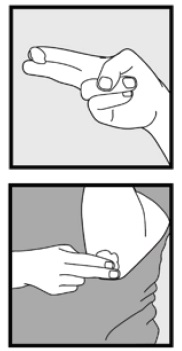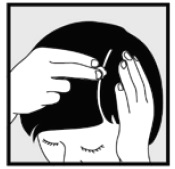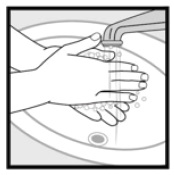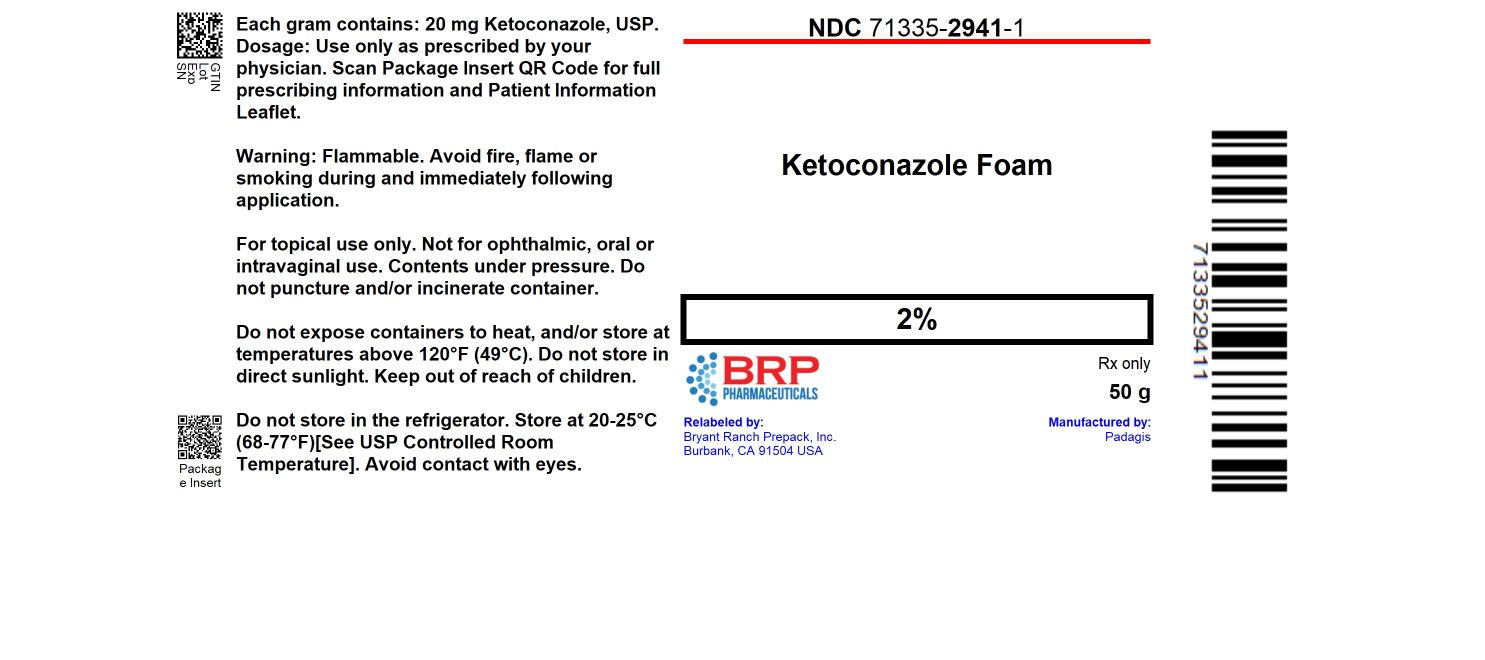 DRUG LABEL: ketoconazole
NDC: 71335-2941 | Form: AEROSOL, FOAM
Manufacturer: Bryant Ranch Prepack
Category: prescription | Type: HUMAN PRESCRIPTION DRUG LABEL
Date: 20251024

ACTIVE INGREDIENTS: KETOCONAZOLE 2 g/100 g
INACTIVE INGREDIENTS: CETYL ALCOHOL; CITRIC ACID MONOHYDRATE; TERT-BUTYL ALCOHOL; ALCOHOL; BRUCINE SULFATE; POLYSORBATE 60; POTASSIUM CITRATE; PROPYLENE GLYCOL; WATER; STEARYL ALCOHOL; BUTANE; PROPANE

HIGHLIGHTS OF PRESCRIBING INFORMATION

These highlights do not include all the information needed to use KETOCONAZOLE FOAM safely and effectively. See full prescribing information for KETOCONAZOLE FOAM.
KETOCONAZOLE foam, 2%
For topical use
Initial U.S. Approval: 1981

1 INDICATIONS AND USAGE

Ketoconazole foam, 2% is indicated for topical treatment of seborrheic dermatitis in immunocompetent patients 12 years of age and older (1).

Limitations of Use

Safety and efficacy of ketoconazole foam, 2% for treatment of fungal infections have not been established.

2 DOSAGE AND ADMINISTRATION

- Ketoconazole foam, 2% should be applied to the affected area(s) twice daily for four weeks (2).
- Ketoconazole foam, 2% is not for ophthalmic, oral, or intravaginal use (2).

3 DOSAGE FORMS AND STRENGTHS

Foam: 2% ketoconazole in 50 g and 100 g containers (3).

4 CONTRAINDICATIONS

None.

5 WARNINGS AND PRECAUTIONS

- Ketoconazole foam, 2% may result in contact sensitization, including photoallergenicity (5.1, 6.2).
- The contents of ketoconazole foam, 2% are flammable. Avoid fire, flame, or smoking during and immediately following application. (5.2).

6 ADVERSE REACTIONS

The most common adverse reactions observed in clinical studies (incidence >1%) were application site burning and application site reaction (6.1).

To report SUSPECTED ADVERSE REACTIONS, contact Padagis® at 1-866-634-9120 or FDA at 1-800-FDA-1088 or www.fda.gov/medwatch.

FULL PRESCRIBING INFORMATION

1 INDICATIONS AND USAGE

Ketoconazole foam, 2% is indicated for the topical treatment of seborrheic dermatitis in immunocompetent patients 12 years of age and older.

Limitations of Use

Safety and efficacy of ketoconazole foam, 2% for treatment of fungal infections have not been established.

2 DOSAGE AND ADMINISTRATION

Ketoconazole foam, 2% should be applied to the affected area(s) twice daily for four weeks.

Hold the container upright, and dispense ketoconazole foam, 2% into the cap of the can or other cool surface in an amount sufficient to cover the affected area(s). Dispensing directly onto hands is not recommended, as the foam will begin to melt immediately upon contact with warm skin. Pick up small amounts of ketoconazole foam, 2% with the fingertips, and gently massage into the affected area(s) until the foam disappears. For hair-bearing areas, part the hair, so that ketoconazole foam, 2% may be applied directly to the skin (rather than on the hair).

Avoid contact with the eyes and other mucous membranes. Ketoconazole foam, 2% is not for ophthalmic, oral or intravaginal use.

3 DOSAGE FORMS AND STRENGTHS

Ketoconazole foam, 2% contains 20 mg of ketoconazole, USP per gram, supplied in 50 g and 100 g containers.

4 CONTRAINDICATIONS

None.

5 WARNINGS AND PRECAUTIONS

5.1 Contact Sensitization

Ketoconazole foam, 2% may result in contact sensitization, including photoallergenicity [see Adverse Reactions (6.2)].

5.2 Flammable Contents

The contents of ketoconazole foam, 2% include alcohol and propane/butane, which are flammable. Avoid fire, flame and/or smoking during and immediately following application. Do not puncture and/or incinerate the containers. Do not expose containers to heat and/or store at temperatures above 120°F (49°C).

5.3 Systemic Effects

Hepatitis has been seen with orally administered ketoconazole (1:10,000 reported incidence). Lowered testosterone and ACTH–induced corticosteroid serum levels have been seen with high doses of orally administered ketoconazole. These effects have not been seen with topical ketoconazole.

6 ADVERSE REACTIONS

6.1 Clinical Trials Experience

Because clinical trials are conducted under widely varying conditions, adverse reaction rates observed in the clinical trials of a drug cannot be directly compared to rates in the clinical trials of another drug, and may not reflect the rates observed in practice. The adverse reaction information from clinical trials does, however, provide a basis for identifying the adverse reactions that appear to be related to drug use and for approximating rates.

The safety data presented in Table 1 reflect exposure to ketoconazole foam, 2% in 672 subjects, 12 years and older with seborrheic dermatitis. Subjects applied ketoconazole foam, 2% or vehicle foam twice daily for 4 weeks to affected areas on the face, scalp, and/or chest. Adverse reactions occurring in > 1% of subjects are presented in Table 1.

Table 1: Adverse Reactions Reported by > 1% Subjects in Clinical Trials

Adverse Reactions | Ketoconazole Foam, 2%; N = 672; n (%) | Vehicle Foam; N = 497; n (%)
Subjects with an Adverse Reaction | 188 (28%) | 122 (25%)
Application site burning | 67 (10%) | 49 (10%)
Application site reaction | 41 (6%) | 24 (5%)

Application site reactions that were reported in <1% of subjects were dryness, erythema, irritation, paresthesia, pruritus, rash and warmth.

6.2 Dermal Safety Studies

In a photoallergenicity study, 9 of 53 subjects (17%) had reactions during the challenge period at both the irradiated and non-irradiated sites treated with ketoconazole foam, 2%. Ketoconazole foam, 2% may cause contact sensitization.

6.3 Postmarketing Experience

The following adverse events have been identified during postmarketing use of ketoconazole foam, 2%:

Gastrointestinal disorders: Cheilitis

General disorders and administration site conditions: Application site pain and application site burn

Skin and subcutaneous tissue disorders: Skin burning sensation and erythema

Because these events are reported voluntarily from a population of uncertain size, it is not always possible to reliably estimate their frequency or establish a causal relationship to drug exposure.

8 USE IN SPECIFIC POPULATIONS

8.1 Pregnancy

Risk Summary

There are no available data on ketoconazole foam, 2% use in pregnant women to identify a drug-associated risk of major birth defects, miscarriage or adverse maternal or fetal outcomes. No reproductive studies in animals have been performed with ketoconazole foam, 2%. In animal reproduction studies with pregnant mice, rats and rabbits both embryotoxic and developmental effects (structural abnormalities) were observed following oral dosing of ketoconazole during organogenesis. Assuming equivalent systemic absorption of topical and oral ketoconazole doses and a ketoconazole foam, 2% maximum recommended human dose (MRHD) of 8 grams (equivalent to 160 mg ketoconazole), embryotoxic effects were observed at 0.8 to 2.4 times the MRHD and developmental effects were observed at 4.8 times the MRHD [see Data].

The background risk of major birth defects and miscarriage for the indicated population is unknown. All pregnancies have a background risk of birth defect, loss, or other adverse outcomes. In the U.S. general population, the estimated background risk of major birth defects and miscarriage in clinically recognized pregnancies is 2 to 4% and 15 to 20%, respectively.

Data

Animal Data

The animal multiples of human exposure calculations are based on body surface area (BSA) comparisons of oral doses administered to animals and a ketoconazole foam, 2% maximum recommended human dose (MRHD) of 8 grams (equivalent to 2.67 mg ketoconazole/kg/day for a 60 kg individual or 98.8 mg ketoconazole/m^2/day).

Embryofetal development studies have been conducted in mice, rats and rabbits with orally administered ketoconazole. When orally administered to mice on gestational days 6 through 18 (covering the period of organogenesis), ketoconazole was embryotoxic (25 mg/kg and higher; 0.8 times the MRHD based on BSA comparisons) with a high incidence of resorptions, increased number of stillbirths and delayed parturition. Delays in maturation were also observed. There was no evidence of maternal toxicity or malformations at up to 50 mg/kg (1.5 times the MRHD based on BSA comparisons). No treatment related developmental effects were observed at 10 mg/kg (0.3 times the MRHD based on BSA comparisons).

In the presence of maternal toxicity in rats, orally administered ketoconazole was both embryotoxic (40 mg/kg and higher; 2.4 times the MRHD based on BSA comparisons), including increased resorbed fetuses and stillbirths, and teratogenic (80 mg/kg and higher; 4.8 times the MRHD based on BSA comparisons), including syndactylia, oligodactylia, waved ribs and cleft palate. Additionally, 100 mg/kg (6 times the MRHD based on BSA comparisons) ketoconazole orally administered on a single day during gestation (gestational days 9 through 12) was embryotoxic (increased resorptions). This same oral dose given on gestation day 12, 13, 14 or 15 induced external malformations including cleft palate, micromelia and digital anomalies (brachydactyly, ectrodactyly, syndactyly).

In pregnant rabbits orally administered ketoconazole, evidence of embryotoxicity (increased resorptions) was observed at 10 mg/kg (1.2 times the MRHD based on BSA comparisons) and higher and an increased incidence of skeletal abnormalities was observed at 40 mg/kg (4.8 times the MRHD based on BSA comparisons).

8.2 Lactation

Risk Summary

There is no information available on the presence of ketoconazole in human milk, or the effects on the breastfed child, or the effects on milk production after topical application of ketoconazole foam, 2% to women who are breastfeeding. In animal studies ketoconazole was found in milk following oral administration. The developmental and health benefits of breastfeeding should be considered along with the mother’s clinical need for ketoconazole foam, 2% and any potential adverse effects on the breastfed infant from ketoconazole foam, 2% or from the underlying maternal condition.

8.3 Females and Males of Reproductive Potential

Infertility

In animal fertility studies in rats and dogs, administration of oral doses of ketoconazole between 3-day and 3-month periods resulted in infertility that was reversible [see Nonclinical Toxicology (13.1)].

8.4 Pediatric Use

The safety and effectiveness of ketoconazole foam, 2% in pediatric patients less than 12 years of age have not been established.

Of the 672 subjects treated with ketoconazole foam, 2% in the clinical trials, 44 (7%) were from 12 to 17 years of age. [See Clinical Studies (14)].

8.5 Geriatric Use

Of the 672 subjects treated with ketoconazole foam, 2% in the clinical trials, 107 (16%) were 65 years and over.

Clinical trials of ketoconazole foam, 2% did not include sufficient numbers of subjects aged 65 and over to determine whether they respond differently than younger subjects.

11 DESCRIPTION

Ketoconazole foam, 2% contains 2% ketoconazole USP, an antifungal agent, in a thermolabile hydroethanolic foam for topical application.

The chemical name for ketoconazole is piperazine, 1-acetyl-4-[4-[[2-(2,4-dichlorophenyl)-2-(1H-imidazol-1-ylmethyl)-1,3-dioxolan-4-yl]methoxy]phenyl]-, cis- with the molecular formula C26H28Cl2N4O4 and a molecular weight of 531.43.

The following is the chemical structure:

Ketoconazole foam, 2% contains 20 mg ketoconazole per gram in a thermolabile hydroethanolic foam vehicle consisting of cetyl alcohol, citric acid, ethanol 58%, polysorbate 60, potassium citrate, propylene glycol, purified water, and stearyl alcohol pressurized with a hydrocarbon (propane/butane) propellant.

12 CLINICAL PHARMACOLOGY

12.1 Mechanism of Action

The mechanism of action of ketoconazole in the treatment of seborrheic dermatitis is not known.

12.2 Pharmacodynamics

The pharmacodynamics of ketoconazole foam, 2% has not been established.

12.3 Pharmacokinetics

In a bioavailability study, 12 subjects with moderate to severe seborrheic dermatitis applied 3 g of ketoconazole foam, 2% twice daily for 4 weeks. Circulating plasma levels of ketoconazole were < 6 ng/mL for a majority of subjects (75%), with a maximum level of 11 ng/mL observed in one subject.

12.4 Microbiology

Ketoconazole is an antifungal agent which inhibits the in vitro synthesis of ergosterol, a key sterol in the cell membrane of Malassezia furfur. The clinical significance of antifungal activity in the treatment of seborrheic dermatitis is not known.

13 NONCLINICAL TOXICOLOGY

13.1 Carcinogenesis, Mutagenesis, Impairment of Fertility

Long-term animal studies have not been performed to evaluate the carcinogenic or photo-carcinogenic potential of ketoconazole foam, 2%.

In oral carcinogenicity studies in mice (18-months) and rats (24-months) at dose levels of 5, 20 and 80 mg/kg/day ketoconazole was not carcinogenic. The high dose in these studies was approximately 2.4 to 4.8 times the MRHD based on BSA comparisons. In a bacterial reverse mutation assay, ketoconazole did not express any mutagenic potential. In three in vivo assays (sister chromatid exchange in humans, dominant lethal and micronucleus tests in mice), ketoconazole did not exhibit any genotoxic potential.

In animal fertility studies, oral ketoconazole impaired both male and female fertility in rats in a dose and duration dependent manner. In females, oral doses up to 40 mg/kg (2.4 times the MRHD based on BSA comparisons) had no effect on fertility, while doses of 75 mg/kg (4.5 times the MRHD based on BSA comparisons) and higher decreased the pregnancy rate and number of implantation sites. In male rats, oral dosing at 200 mg/kg/day (12 times the MRHD based on BSA comparisons) for three days decreased fertility and 400 mg/kg/day (24 times the MRHD based on BSA comparisons) for three days resulted in a complete loss of fertility. When administered for longer durations (up to 3 months), decreased fertility in male rats was observed at doses as low as 24 mg/kg/day (1.4 times the MRHD based on BSA comparisons). In male beagle dogs, an oral dose of 25 mg/kg/day ketoconazole for up to 4 weeks (5.2 times the MRHD based on BSA comparisons) resulted in decreased sperm motility, decreased sperm count, increased abnormal sperm and atrophy of the testes. These effects were reversed subsequent to withdrawal of treatment.

14 CLINICAL STUDIES

The safety and efficacy of ketoconazole foam, 2% were evaluated in a randomized, double-blind, vehicle-controlled trial in subjects 12 years and older with mild to severe seborrheic dermatitis. In the trial, 427 subjects received ketoconazole foam, 2% and 420 subjects received vehicle foam. Subjects applied ketoconazole foam, 2% or vehicle foam twice daily for 4 weeks to affected areas on the face, scalp, and/or chest. The overall disease severity in terms of erythema, scaling, and induration was assessed at Baseline and week 4 on a 5-point Investigator’s Static Global Assessment (ISGA) scale.

Treatment success was defined as achieving a Week 4 (end of treatment) ISGA score of 0 (clear) or 1 (majority of lesions have individual scores for scaling, erythema, and induration that averages 1 [minimal or faint]) and at least two grades of improvement from baseline. The results are presented in Table 2. The database was not large enough to assess whether there were differences in effects in age, gender, or race subgroups.

Table 2: Efficacy Results

Number of Subjects | Ketoconazole Foam, 2%; N = 427; n (%) | Vehicle Foam; N = 420; n (%)
Subjects Achieving Treatment Success | 239 (56%) | 176 (42%)

16 HOW SUPPLIED/STORAGE AND HANDLING

Ketoconazole Foam, 2% contains 20 mg of ketoconazole, USP per gram. The thermolabile hydroethanolic foam is available as follows:

NDC: 71335-2941-1: 50 g aluminum can

Store at 20° to 25°C (68° to 77°F). [See USP Controlled Room Temperature.]

Do not store under refrigerated conditions.

Contents are flammable. Do not expose containers to heat and/or store at temperatures above 49°C (120°F). Do not store in direct sunlight.

Contents under pressure. Do not puncture and/or incinerate container.

Keep out of reach of children.

Repackaged/Relabeled by:
Bryant Ranch Prepack, Inc.
Burbank, CA 91504

17 PATIENT COUNSELING INFORMATION

See FDA-approved patient labeling (Patient Package Insert).

Instruct patients on a proper use of ketoconazole foam, 2%.

- Avoid fire, flame and/or smoking during and immediately following application.
- Do not apply ketoconazole foam, 2% directly to hands. Dispense onto a cool surface, and apply to the affected areas using the fingertips.
- Wash their hands after application
- Ketoconazole foam, 2% may cause skin irritation (application site burning and/or reactions)
- Instruct a patient to contact a health care provider if the area of application shows signs of increased irritation and report any signs of adverse reactions.

Manufactured by Padagis®

Yeruham, Israel

www.padagis.com

Rev 02-24

5K200 RC PH6

Product of India

PATIENT INFORMATION

Ketoconazole Foam, 2%

Important Information: Ketoconazole foam, 2% is for use on the skin only. Do not use ketoconazole foam, 2% in your eyes, mouth or vagina.

What is ketoconazole foam, 2%?

Ketoconazole foam, 2% is a prescription medicine used on the skin (topical) to treat seborrheic dermatitis in people 12 years of age and older with a normal immune system.

It is not known if ketoconazole foam, 2% is safe and effective when used to treat fungal infections.

It is not known if ketoconazole foam, 2% is safe and effective in children less than 12 years of age.

Before using ketoconazole foam, 2%, tell your healthcare provider about all of your medical conditions, including if you:

- are pregnant or plan to become pregnant. It is not known if ketoconazole foam, 2% will harm your unborn baby.
- are breastfeeding or plan to breastfeed. It is not known if ketoconazole passes into your breast milk. Talk to your healthcare provider about the best way to feed your baby during treatment with ketoconazole foam, 2%.

Tell your healthcare provider about all the medicines you take, including prescription and over-the-counter medicines, vitamins, and herbal supplements.

How should I use ketoconazole foam, 2%?

- Use ketoconazole foam, 2% exactly as your healthcare provider tells you to use it. See the detailed “Instructions for Use” at the end of this leaflet for directions about how to apply ketoconazole foam, 2% the right way.
- Apply ketoconazole foam, 2% to the affected skin area(s) 2 times each day for 4 weeks. You should apply enough ketoconazole foam, 2% to cover the entire affected area(s).
- Talk to your healthcare provider if your skin does not improve after 4 weeks of treatment with ketoconazole foam, 2%.
- Dispense ketoconazole foam, 2% directly into the cap. Do not dispense ketoconazole foam, 2% directly onto your hands, because the foam will begin to melt on contact with warm skin.
- Wash your hands after applying ketoconazole foam, 2%.

What should I avoid while using ketoconazole foam, 2%?

- Ketoconazole foam, 2% is flammable. Avoid fire, flames, or smoking during and right after you apply ketoconazole foam, 2% to your skin.
- Avoid getting ketoconazole foam, 2% in or near your eyes, mouth, lips or vagina. If you get ketoconazole foam, 2% on your lips or in your eyes, mouth or vagina, rinse well with water.

What are the possible side effects of ketoconazole foam, 2%?

Ketoconazole foam, 2% may cause serious side effects, including:

- Skin irritation at the application area(s), including skin reactions caused by exposure to light. Tell your healthcare provider if you develop skin irritation during treatment with ketoconazole foam, 2%.

The most common side effects of ketoconazole foam, 2% include, burning, dryness, redness, irritation, numbness, itching, rash and warmth at the application site.

These are not all of the possible side effects of ketoconazole foam, 2%.

Call your doctor for medical advice about side effects. You may report side effects to FDA at 1-800-FDA-1088.

How should I store ketoconazole foam, 2%?

- Store ketoconazole foam, 2% at room temperature between 68°F to 77°F (20°C to 25°C).
- Do not store the ketoconazole foam, 2% can in the refrigerator or freezer.
- Keep ketoconazole foam, 2% away from heat. Never throw the ketoconazole foam, 2% can into a fire, even if the can is empty.
- Do not store ketoconazole foam, 2% at temperatures above 120°F (49°C).
- Do not break through (puncture) the ketoconazole foam, 2% can.
Keep ketoconazole foam, 2% and all medicines out of the reach of children.

General information about the safe and effective use of ketoconazole foam, 2%.

Medicines are sometimes prescribed for purposes other than those listed in a Patient Information leaflet. Do not use ketoconazole foam, 2% for a condition for which it was not prescribed. Do not give ketoconazole foam, 2% to other people, even if they have the same symptoms that you have. It may harm them. You can ask your pharmacist or healthcare provider for information about ketoconazole foam, 2% that is written for health professionals.

What are the ingredients in ketoconazole foam, 2%?

Active ingredient: ketoconazole

Inactive Ingredients: cetyl alcohol, citric acid, ethanol 58%, polysorbate 60, potassium citrate, propylene glycol, purified water, and stearyl alcohol pressurized with a hydrocarbon (propane/butane) propellant

For more information, call Padagis at 1-866-634-9120

This Patient Information leaflet has been approved by the U.S. Food and Drug Administration.

Instructions for Use

Ketoconazole Foam, 2%

Important Information: Ketoconazole foam, 2% is for use on the skin only. Do not use ketoconazole foam, 2% in your eyes, mouth or vagina.

Step 1: Remove the clear cap from the ketoconazole foam, 2% can.

Step 2: Hold the can upright and firmly press the nozzle to dispense ketoconazole foam, 2% into the clear cap.
2. Dispense enough ketoconazole foam, 2% to cover the entire affected area(s).

- If the can seems warm or the foam seems runny, run the can under cold water.

Step 3: Pick up small amounts of ketoconazole foam, 2% with your fingertips and gently rub the foam into the affected area(s) until the foam disappears.

- If you are treating areas such as your scalp, part the hair so that ketoconazole foam, 2% may be applied directly to the skin.

Step 4: Wash your hands after applying ketoconazole foam, 2%.
2. Throw away any of the unused medicine that is left in the cap.

How should I store ketoconazole foam, 2%?

- Store ketoconazole foam, 2% at room temperature between 68°F to 77°F (20°C to 25°C).
- Do not store the ketoconazole foam, 2% can in the refrigerator or freezer.
- Keep ketoconazole foam, 2% away from heat. Never throw the can into a fire, even if the can is empty.
- Do not store ketoconazole foam, 2% at temperatures above 120°F (49°C).
- Do not break through (puncture) the ketoconazole foam, 2% can.

Keep ketoconazole foam, 2% and all medicines out of the reach of children.

This Instructions for Use has been approved by the U.S. Food and Drug Administration.

Rx Only

Manufactured by Padagis®

Yeruham, Israel

www.padagis.com

Rev 02-24

5K200 RC PH6

Product of India

PACKAGE LABEL

Ketoconazole 2% Foam #50